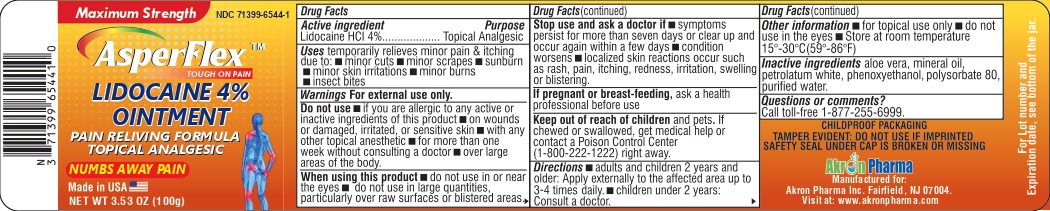 DRUG LABEL: Lidocaine
NDC: 71399-6544 | Form: OINTMENT
Manufacturer: Akron Pharma Inc.
Category: otc | Type: HUMAN OTC DRUG LABEL
Date: 20240918

ACTIVE INGREDIENTS: LIDOCAINE 4 g/1 1
INACTIVE INGREDIENTS: POLYSORBATE 80; PHENOXYETHANOL; WATER; MINERAL OIL; WHITE PETROLATUM; ALOE VERA WHOLE

AsperFlex (Lidocaine 4% Ointment)

Active ingredient

Lidocaine HCL 4%

Purpose

Topical Analgesic

Uses

Temporarily relieves minor pain & itching due to:

- minor cuts
- minor scrapes
- sunburn
- minor skin irritations
- minor burns
- insect bites

Warnings

For external use only

Do not use

- if you are allergice to any active or inactive ingredients of this product
- on wonds or damaged, irritated, or sensitive skin
- with any other topical anesthetic
- for more than one week without constulting a doctor
- over large areas of the body

When using this product

- do not use in or near the eyes
- do not use in large quantities, particularly over raw surfaces or blistered areas

Stop use and ask a doctor if

- symptoms presist for more than seven days or clear up and occur again within a few days
- Condition worsens
- localized skin reactions occur such as rash, pain, itching, readness, irritation, swelling or blistering

PREGNANCY OR BREAST FEEDING

If pregnant or breast-feeding, ask a health professional before use

Keep out of reach of children and pets. If chewed or swallowed, get medical help or contact a Poison Control Center (1-800-222-1222) right away.

Directions

- adults and children 2 years and older: Apply externally to the affected area up to 3-4 times daily.
- Children under 2 years: Consult a doctor.

Other information

- for topical use only
- do not use in the eyes
- Store are room temperature 15°-30°C (59°-86°F)

Inactive ingredients

aloe vera, mineral oil, petrolatum white, phenoxyethanol, polysorbate 80, purified water.

Questions or comments?

Call toll-free 1-877-255-6999

Childproof Packaging

Tamper Evident: Do not use if imprinted safety seal under cap is broken or missing

Manufactured for:

Akron Pharma Inc.

Fairfield, Nj 07004

Visit at: www.akronpharma.com

PACKAGE LABEL

Maximun Strength

NDC 71399-6544-1

AsperFlex™

Touch on Pain

Lidocaine 4% Ointment

Pain reliving Formula

Topical Analgesic

Numbs Away Pain

Made in the USA

NET WT 3.53 OZ (100g)